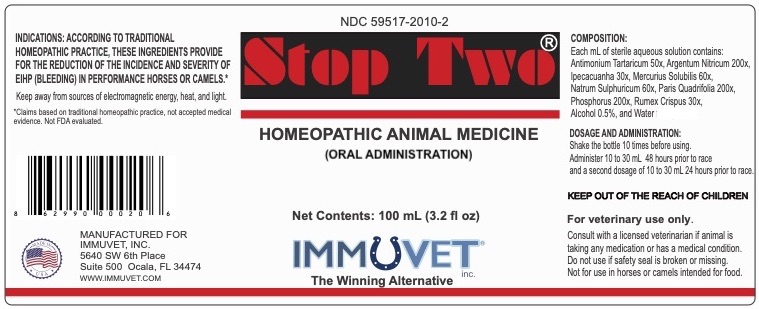 DRUG LABEL: Stop Two
NDC: 59517-2010 | Form: LIQUID
Manufacturer: Immuvet, Inc.
Category: homeopathic | Type: OTC ANIMAL DRUG LABEL
Date: 20251104

ACTIVE INGREDIENTS: ANTIMONY POTASSIUM TARTRATE 50 [hp_X]/1 mL; SILVER NITRATE 200 [hp_X]/1 mL; IPECAC 30 [hp_X]/1 mL; MERCURIUS SOLUBILIS 60 [hp_X]/1 mL; SODIUM SULFATE 60 [hp_X]/1 mL; PARIS QUADRIFOLIA 200 [hp_X]/1 mL; PHOSPHORUS 15 [hp_X]/1 mL; RUMEX CRISPUS ROOT 30 [hp_X]/1 mL
INACTIVE INGREDIENTS: ALCOHOL; WATER

Stop Two

PURPOSE

ACCORDING TO HOMEOPATHIC INDICATIONS, THE ACTIVE INGREDIENTS MAY HELP TO REDUCE THE INCIDENCE AND SEVERITY OF EIPH (BLEEDING) IN PERFORMANCE HORSES.**

DIRECTIONS

RECOMMENDED USE:
First dosage 10-30 cc 48 hrs to race
Second dosage 10-30 cc 24 hours to race
Keep away from sources of energy, heat and light.

ACTIVE INGREDIENTS

Antimon Tartaricum 50x
Argentum Nitricum 200x
Ipecacuanha 30x
Mercurius Solubilis 60x
Natrum Sulph 60x
Paris Quadrifolia 200x
Phosphorus 15x, 200x
Rumex Crispus 30x

INACTIVE INGREDIENTS

Distilled water, Alcohol 5%

WARNINGS

Do not use if seal is broken.
For Oral Veterinary Use Only.
Not for use in Horses intended for food.
If problems persist, contact a veterinarian.
Keep out of reach of children.

OTHER INFORMATION

**THESE STATEMENTS HAVE NOT BEEN EVALUATED BY THE FDA.
THIS PRODUCT IS NOT INTENDED TO DIAGNOSE, TREAT, CURE OR PREVENT ANY DISEASE.